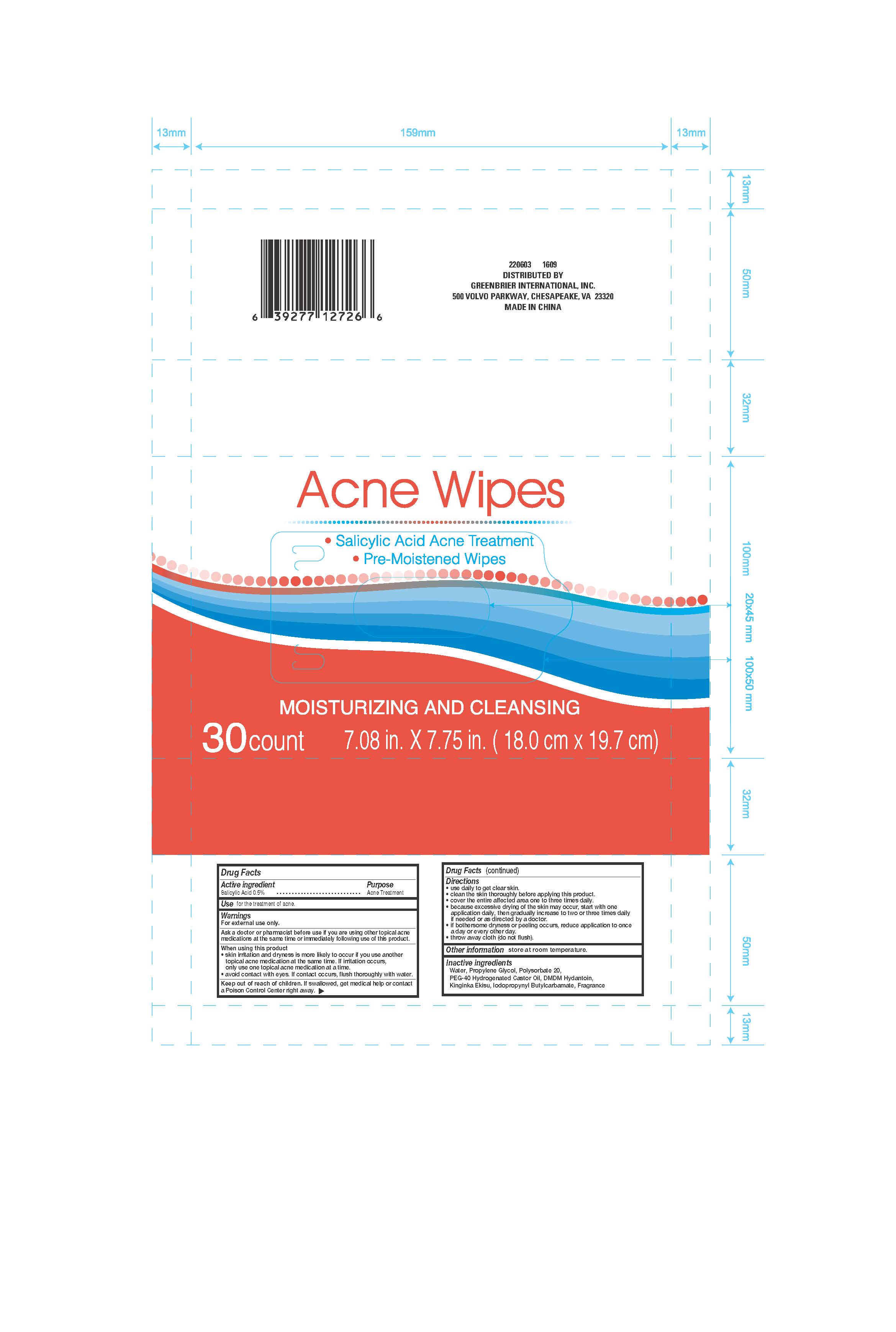 DRUG LABEL: Acne Wipes
NDC: 44019-006 | Form: SWAB
Manufacturer: Yinjing Medical Technology (Shanghai) Co., Ltd.
Category: otc | Type: HUMAN OTC DRUG LABEL
Date: 20160813

ACTIVE INGREDIENTS: SALICYLIC ACID .5 g/100 mL
INACTIVE INGREDIENTS: WATER; PROPYLENE GLYCOL; polysorbate 20; POLYOXYL 40 HYDROGENATED CASTOR OIL; DMDM HYDANTOIN; IODOPROPYNYL BUTYLCARBAMATE

Active ingredient

Salicylic Acid 0.5%

Purpose

Acne Treatment

INDICATIONS AND USAGE

Use for the treatment of acne

Warnings

For external use only.

Ask a doctor or pharmacist before use if you ar eusing other topical acne

medications at the same time or immediately following use of this product.

When using this product

-skin irritation and dryness is more likely to occur if you use another

topical acne medication at the same time. If irritation occurs,

only use one topical acne medication at a time.

-avoid contact with eyes. If contact occurs, flush thoroughly with water.

Keep out of reach of children. If swallowed, get medical help or contact

a Poison Control Center right away.

Directions

-use daily to get clear skin.

-clean the skin thoroughly before applying this product.

-cover the entire affected area one to three times daily.

-because excessive drying of the skinmay occur, start with one

application daily, then gradually increase to two or three times daily

if needed or as directed by a doctor.

-if bothersome dryness or peeling occurs, reduce application to once

a day or every other day.

-throw away cloth (do not flush).

Other information store at room temperature.

Inactive ingredients

Water, Propylene Glycol, Polysorbate 20,

PEG-40 Hydrogenated Castor Oil, DMDM Hydantoin,

Kinginka Ekisu, Iodopropynol Butylcarbamate, Frangrance